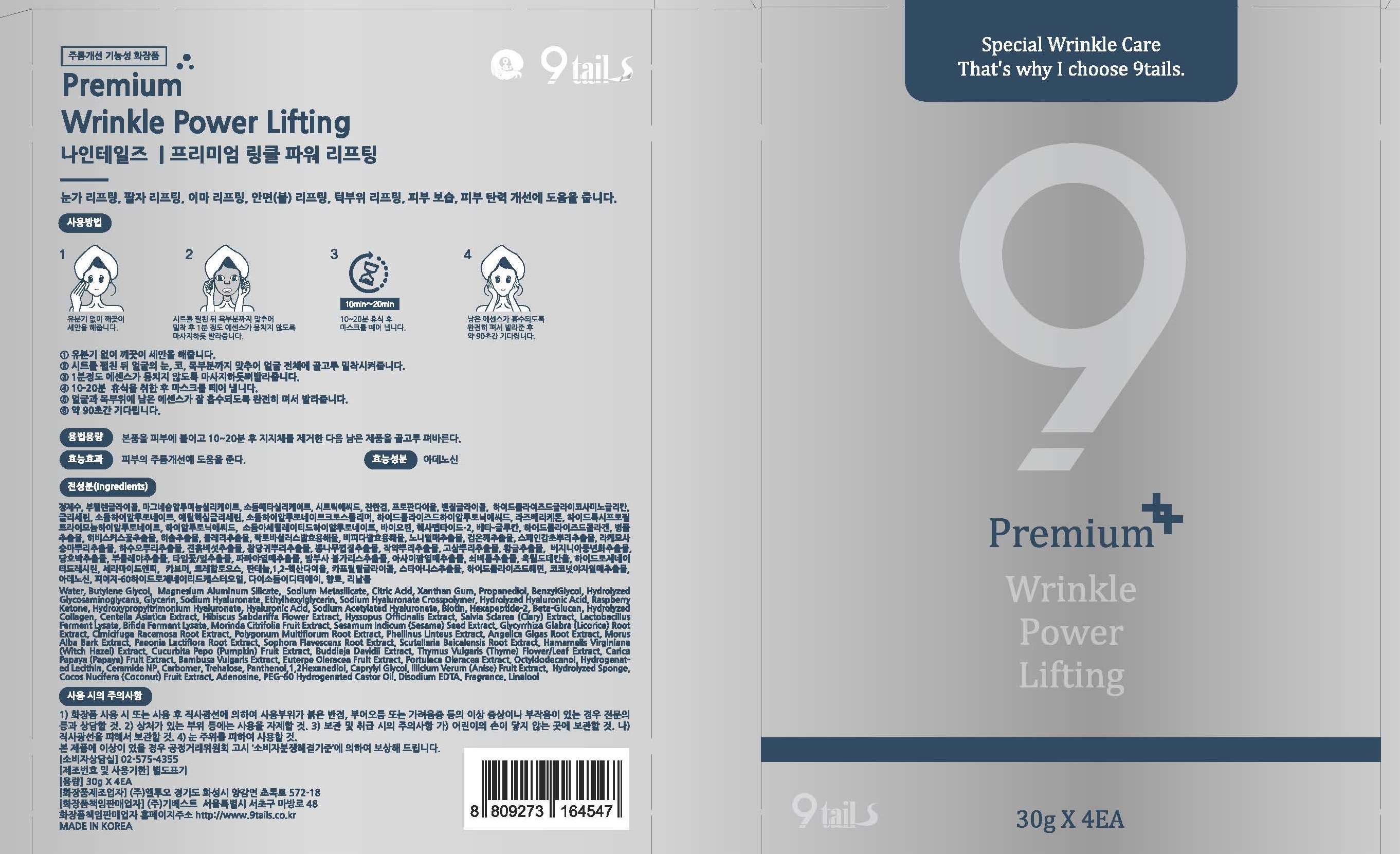 DRUG LABEL: 9tails Premium Wrinkle Power Lifting
NDC: 73420-0001 | Form: LIQUID
Manufacturer: ELUO.CO.,Ltd.
Category: otc | Type: HUMAN OTC DRUG LABEL
Date: 20191028

ACTIVE INGREDIENTS: ADENOSINE 0.04 g/100 g
INACTIVE INGREDIENTS: GLYCERIN; WATER

GIBEST / ELUO - Wrinkle Power Filling

ACTIVE INGREDIENT

adenosine

INACTIVE INGREDIENT

water, glycerin, butylene glycol, etc

PURPOSE

For wrinkle care

keep out of reach of the children

INDICATIONS AND USAGE

Apply this product to skin, remove the support after 10-20 minutes, and spread the remaining product evenly.

WARNINGS

1. If you have any abnormal symptoms or side effects such as red spots, swelling or itching, etc. when using cosmetics or by direct sunlight after use, consult a specialist.
2. Do not use on wounded area.
3. Precautions for Storage and Handling

- 1) Keep out of reach of children
- 2) Keep away from direct sunlight.
- 3) Avoid using around the eyes

DOSAGE AND ADMINISTRATION

for external use only